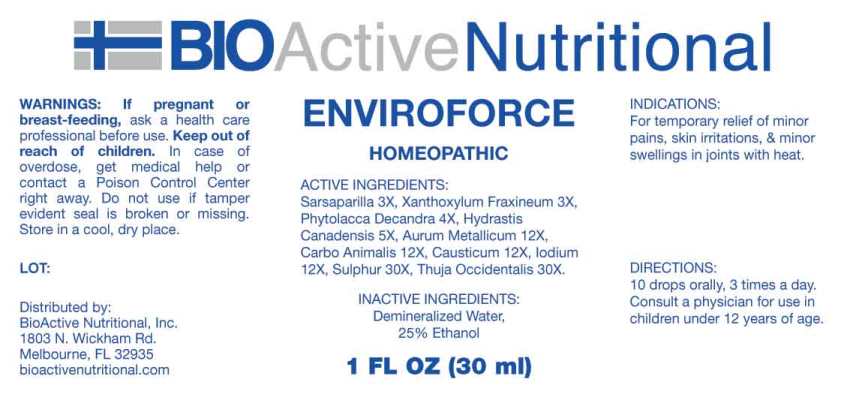 DRUG LABEL: Enviroforce
NDC: 43857-0630 | Form: LIQUID
Manufacturer: BioActive Nutritional, Inc.
Category: homeopathic | Type: HUMAN OTC DRUG LABEL
Date: 20230410

ACTIVE INGREDIENTS: SMILAX ORNATA ROOT 3 [hp_X]/1 mL; ZANTHOXYLUM AMERICANUM BARK 3 [hp_X]/1 mL; PHYTOLACCA AMERICANA ROOT 4 [hp_X]/1 mL; GOLDENSEAL 5 [hp_X]/1 mL; GOLD 12 [hp_X]/1 mL; CARBO ANIMALIS 12 [hp_X]/1 mL; CAUSTICUM 12 [hp_X]/1 mL; IODINE 12 [hp_X]/1 mL; SULFUR 30 [hp_X]/1 mL; THUJA OCCIDENTALIS LEAFY TWIG 30 [hp_X]/1 mL
INACTIVE INGREDIENTS: WATER; ALCOHOL

DRUG FACTS:

ACTIVE INGREDIENTS:

Sarsaparilla 3X, Xanthoxylum Fraxineum 3X, Phytolacca Decandra 4X, Hydrastis Canadensis 5X, Aurum Metallicum 12X, Carbo Animalis 12X, Causticum 12X, Iodium 12X, Sulphur 30X, Thuja Occidentalis 30X.

PURPOSE:

For temporary relief of minor pains, skin irritations, & minor swellings in joints with heat.

WARNINGS:

If pregnant or breast-feeding, ask a health care professional before use.

Keep out of reach of children. In case of overdose, get medical help or contact a Poison Control Center right away.

Do not use if tamper evident seal is broken or missing.

Store in a cool, dry place.

KEEP OUT OF REACH OF CHILDREN:

In case of overdose, get medical help or contact a Poison Control Center right away.

DIRECTIONS:

10 drops orally, 3 times a day. Consult a physician for use in children under 12 years of age.

INDICATIONS:

For temporary relief of minor pains, skin irritations, & minor swellings in joints with heat.

INACTIVE INGREDIENTS:

Demineralized Water, 25% Ethanol

QUESTIONS:

Distributed by:

BioActive Nutritional, Inc.

1803 N. Wickham Rd.

Melbourne, FL 32935

bioactivenutritional.com

PACKAGE LABEL DISPLAY:

BioActive Nutritional

ENVIROFORCE

HOMEOPATHIC

1 FL OZ (30 ml)